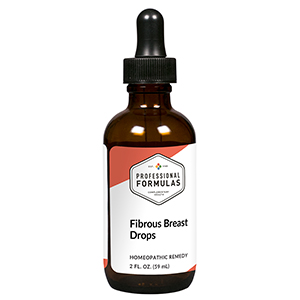 DRUG LABEL: Fibrous Breast Drops
NDC: 63083-2148 | Form: LIQUID
Manufacturer: Professional Complementary Health Formulas
Category: homeopathic | Type: HUMAN OTC DRUG LABEL
Date: 20190815

ACTIVE INGREDIENTS: ECHINACEA ANGUSTIFOLIA WHOLE 1 [hp_X]/59 mL; ARTEMISIA ANNUA FLOWERING TOP 3 [hp_X]/59 mL; PHYTOLACCA AMERICANA ROOT 4 [hp_X]/59 mL; BRYONIA ALBA ROOT 6 [hp_X]/59 mL; BOS TAURUS LYMPH VESSEL 6 [hp_X]/59 mL; SUS SCROFA MAMMARY GLAND 6 [hp_X]/59 mL; HELIANTHEMUM CANADENSE 6 [hp_X]/59 mL; ARNICA MONTANA WHOLE 6 [hp_X]/59 mL; AETHUSA CYNAPIUM WHOLE 12 [hp_X]/59 mL; SANGUINARIA CANADENSIS ROOT 12 [hp_X]/59 mL; OYSTER SHELL CALCIUM CARBONATE, CRUDE 30 [hp_X]/59 mL; CONIUM MACULATUM FLOWERING TOP 30 [hp_X]/59 mL; ONOSMODIUM VIRGINIANUM 30 [hp_X]/59 mL; SCABIES LESION LYSATE (HUMAN) 30 [hp_X]/59 mL
INACTIVE INGREDIENTS: ALCOHOL; WATER

C148

ACTIVE INGREDIENTS

Echinacea angustifolia 1X
Chamomilla 3X
Phytolacca decandra 4X
Bryonia 6X
Chamomilla 6X
Lymph 6X
Mammary 6X
Cistus canadensis 6X, 12X, 30X
Arnica montana 6X, 12X, 30X, 60X
Aethusa cynapium 12X
Sanguinaria canadensis 12X
Calcarea carbonica 30X
Conium maculatum 30X
Onosmodium virginianum 30X
Psorinum 30X, 60X, 100X

QUESTIONS

Professional Formulas

PO Box 2034 Lake Oswego, OR 97035

INDICATIONS

For the temporary relief of swollen, tender, sore, or painful breasts.*

PURPOSE

*Claims based on traditional homeopathic practice, not accepted medical evidence. Not FDA evaluated.

WARNINGS

Consult a doctor if condition worsens or if symptoms persist. Keep out of the reach of children. In case of overdose, get medical help or contact a poison control center right away. If pregnant or breastfeeding, ask a healthcare professional before use.

Keep out of the reach of children.

PREGNANCY OR BREAST FEEDING

If pregnant or breastfeeding, ask a healthcare professional before use.

DIRECTIONS

Place drops under tongue 30 minutes before/after meals. Adults and children 12 years and over: Take 10 drops up to 3 times per day. Consult a physician for use in children under 12 years of age. Not intended for use in infants.

OTHER INFORMATION

Tamper resistant. If seal is broken, do not use. After opening, close container tightly and store at room temperature away from heat.

INACTIVE INGREDIENTS

20% ethanol, purified water.

LABEL

Est 1985

Professional Formulas

Complementary Health

Fibrous Breast Drops

Homeopathic Remedy

2 FL. OZ. (59 mL)